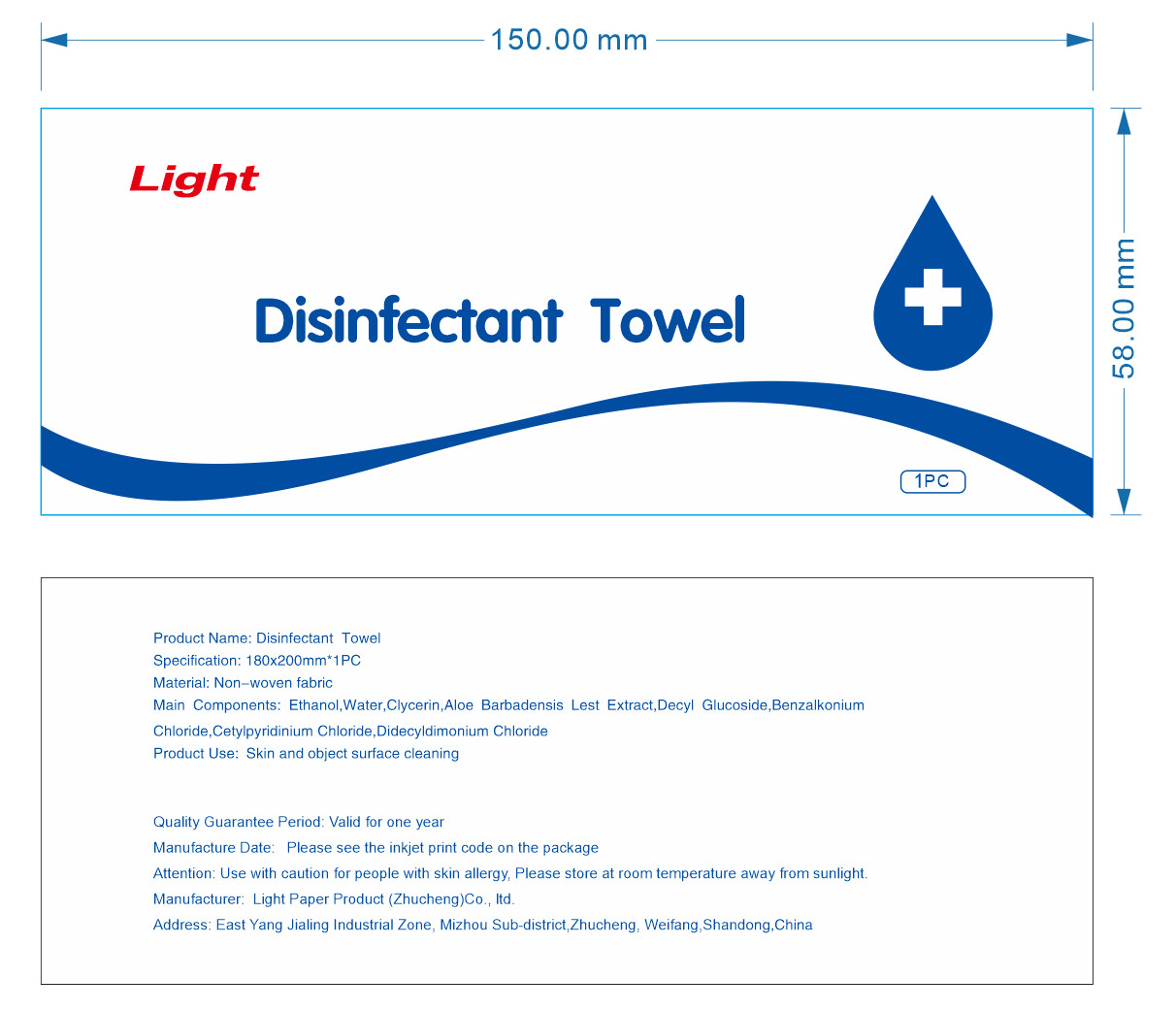 DRUG LABEL: Disinfectant Towel
NDC: 66861-001 | Form: CLOTH
Manufacturer: LIGHT PAPER PRODUCT (ZHUCHENG) CO.LTD
Category: otc | Type: HUMAN OTC DRUG LABEL
Date: 20200615

ACTIVE INGREDIENTS: ALCOHOL 2 mL/1 1
INACTIVE INGREDIENTS: GLYCERIN; WATER; ALOE

DOSAGE AND ADMINISTRATION

temperature storage

INDICATIONS AND USAGE

Tear the package and wipe with a paper towel on the surface of the object

ACTIVE INGREDIENT

ALCOHOL

keep out of reach of children

PURPOSE

Disinfection
Sterilization
No Rinseing

WARNINGS

For external use only. Flammable,keep away from fire or flame.

INACTIVE INGREDIENT

GLYCERIN

ALOE EXTRACT

WATER